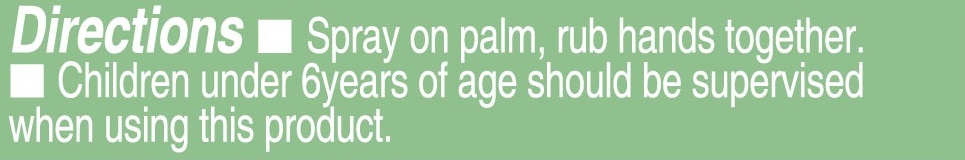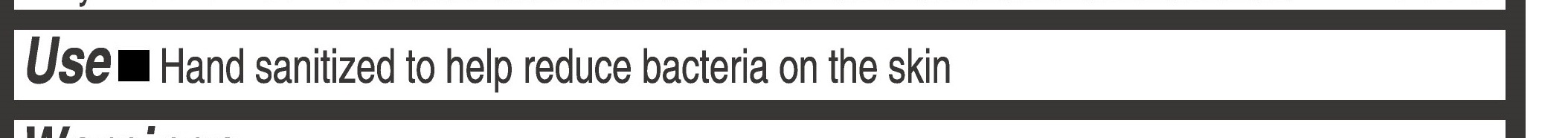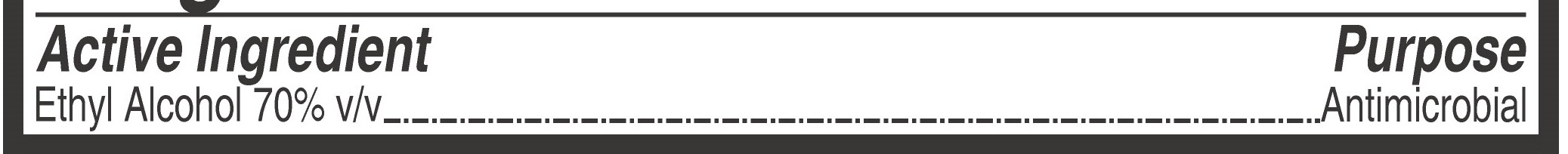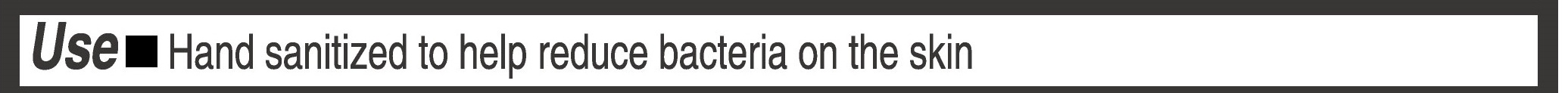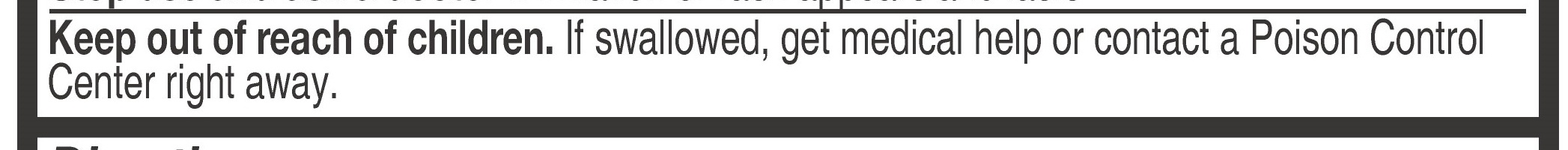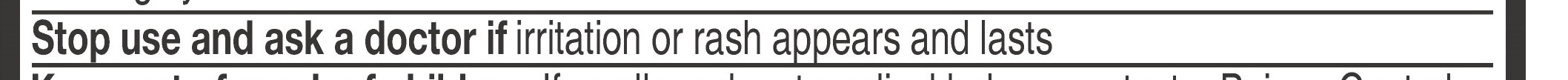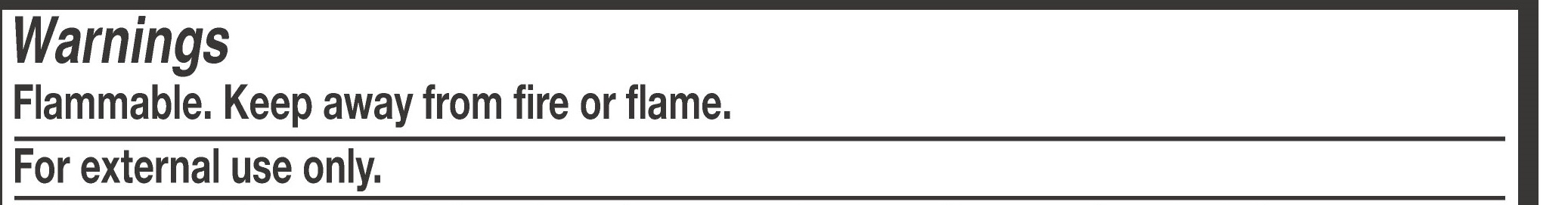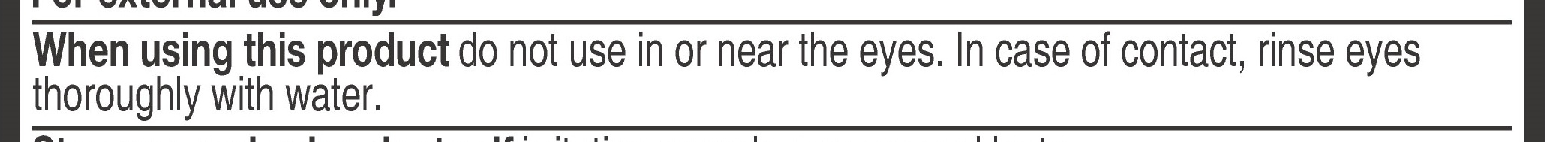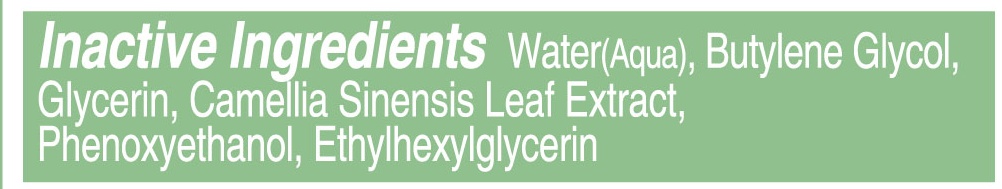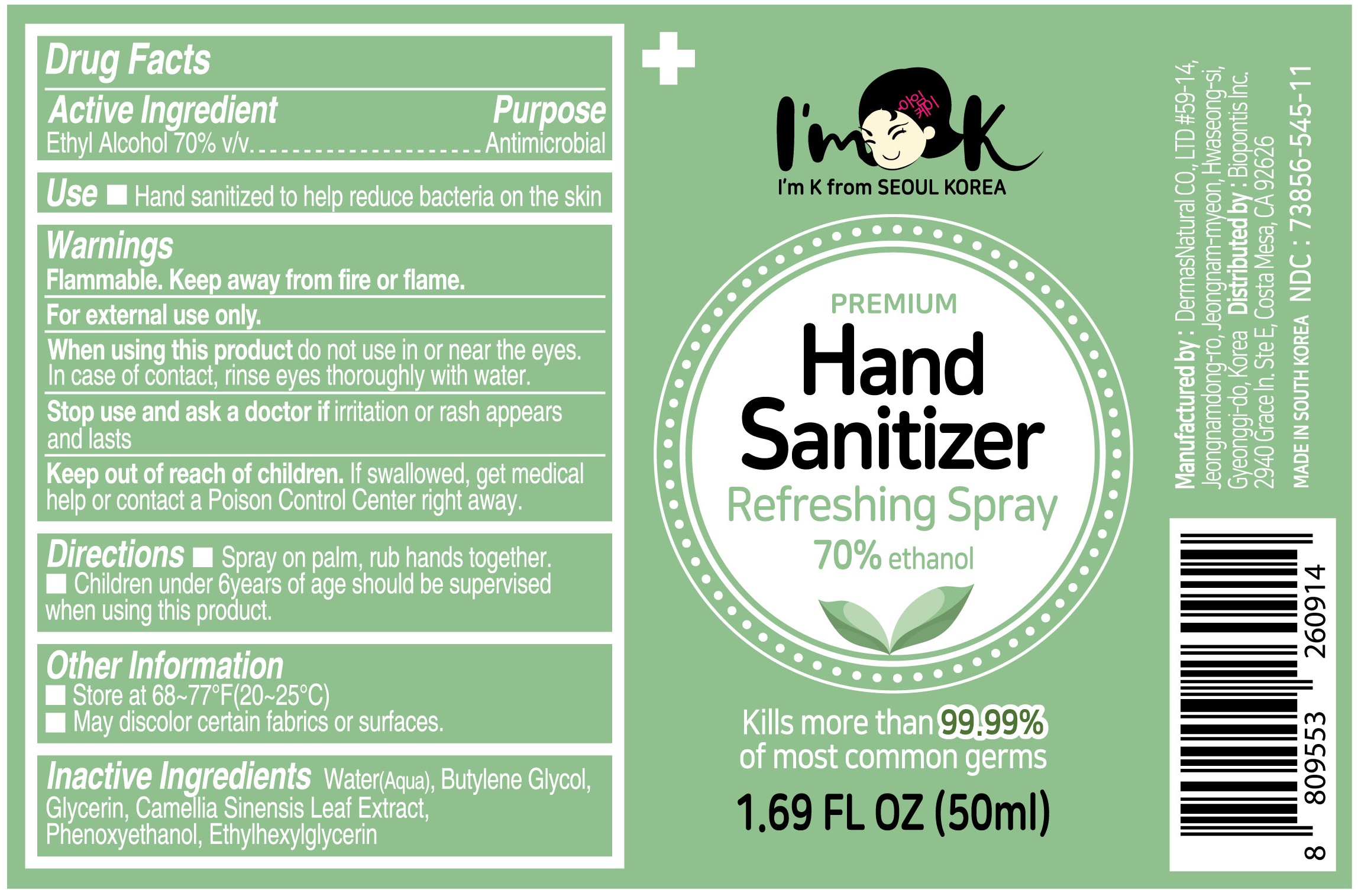 DRUG LABEL: ImK hand sanitizer
NDC: 73856-545 | Form: SPRAY
Manufacturer: Biopontis inc
Category: otc | Type: HUMAN OTC DRUG LABEL
Date: 20200522

ACTIVE INGREDIENTS: ALCOHOL 35 mL/50 mL
INACTIVE INGREDIENTS: ETHYLHEXYLGLYCERIN; PHENOXYETHANOL; WATER; GLYCERIN; GREEN TEA LEAF; BUTYLENE GLYCOL

Active Ingredient

Ethyl Alcohol 70% v/v

Purpose

Antimicrobial

Keep out of reach of children. If swallowed, get medical help or contact a Poison Control Center right away.

Stop use and ask a doctor if irritation or rash appears and lasts

When using this product do not use in or near the eyes. In case of contact, rinse eyes thoroughly with water.

DIrections

Spray on palm, rub hands together

children under 6 years of age should be supervised when using this product

Warning

Flammable. Keep away from fire or flame.

For external use only.

Inactive Ingredients

Water(aqua), Butylene Glycol, Glycerin, Camellia Sinensis Leaf Extract, Phenoxyethanol, Ethylhexylglycerin

Use

Hand sanitized to help reduce bacteria on the skin

Use

Hand sanitized to help reduce bacteria on the skin

Package label